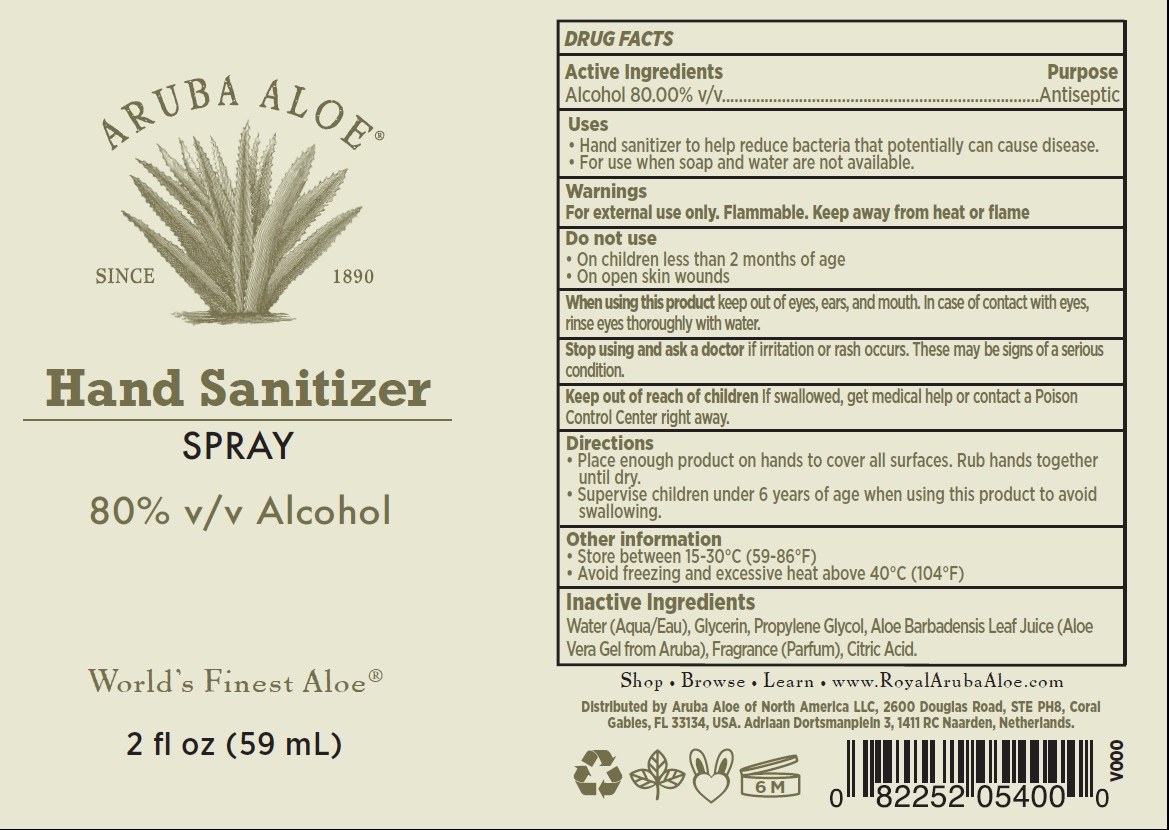 DRUG LABEL: Aruba Aloe Hand Sanitizer
NDC: 53675-213 | Form: CREAM
Manufacturer: Aruba Aloe Balm NV
Category: otc | Type: HUMAN OTC DRUG LABEL
Date: 20250807

ACTIVE INGREDIENTS: ALCOHOL 80 mL/100 mL
INACTIVE INGREDIENTS: WATER; GLYCERIN; PROPYLENE GLYCOL; ALOE VERA LEAF; CITRIC ACID MONOHYDRATE

Aruba Aloe Hand Sanitizer Spray

Active Ingredients

Alcohol 80.00% v/v

Purpose

Antiseptic

Uses

- Hand sanitizer to help reduce bacteria that potentially can cause disease.
- For use when soap and water are not available.

Warnings

For external use only. Flammable. Keep away from heat or flame

Do not use

- On children less than 2 months of age
- On open skin wounds

When using this product

keep out of eyes, ears, and mouth. In case of contact with eyes, rinse eyes thoroughly with water.

Stop use and ask a doctor if

irritation or rash occurs. These may be signs of a serious condition.

Keep out of reach of children.

If swallowed, get medical help or contact a Poison Control Center right away.

Directions

- Place enough product on hands to cover all surfaces. Rub hands together until dry.
- Supervise children under 6 years of age when using this product to avoid swallowing.

Other information

- Store between 15-30°C (59-86°F)
- Avoid freezing and excessive heat above 40°C (104°F)

Inactive Ingredients

Water (Aqua/Eau), Glycerin, Propylene Glycol, Aloe Barbadensis Leaf Juice (Aloe Vera Gel from Aruba), Fragrance (Parfum), Citric Acid.